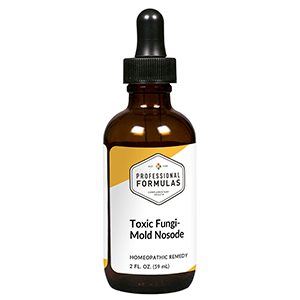 DRUG LABEL: Toxic Fungi-Mold Nosode
NDC: 63083-4018 | Form: LIQUID
Manufacturer: Professional Complementary Health Formulas
Category: homeopathic | Type: HUMAN OTC DRUG LABEL
Date: 20190815

ACTIVE INGREDIENTS: PLEOSPORA HERBARUM 30 [hp_X]/59 mL; ASPERGILLUS FLAVUS 30 [hp_X]/59 mL; CHAETOMIUM GLOBOSUM 30 [hp_X]/59 mL; CLADOSPORIUM SPHAEROSPERMUM 30 [hp_X]/59 mL; RHODOTORULA RUBRA 30 [hp_X]/59 mL; HELMINTHOSPORIUM CARBONUM TOXIN I 30 [hp_X]/59 mL; HISTOPLASMA CAPSULATUM 30 [hp_X]/59 mL; PENICILLIN G 30 [hp_X]/59 mL; STACHYBOTRYS CHARTARUM 30 [hp_X]/59 mL
INACTIVE INGREDIENTS: ALCOHOL; WATER

N18

ACTIVE INGREDIENTS

all the following at 30X, 60X:
Alternaria
Aspergillus mix (aspergillus flavus, fumigatus, glaucus, niger, and nidulans)
Chaetomium sp.
Cladosporium
Cryptococcus neoformans
Helminthosporium
Histoplasma capsulatum
Penicillium notatum
Stachybotrys chartarum

QUESTIONS

Professional Formulas

PO Box 2034 Lake Oswego, OR 97035

INDICATIONS

For the temporary relief of nasal irritation or congestion, cough, shortness of breath, occasional headaches, irritability, or fatigue.*

PURPOSE

*Claims based on traditional homeopathic practice, not accepted medical evidence. Not FDA evaluated.

WARNINGS

If symptoms do not improve or are accompanied by a fever, consult a doctor. Keep out of the reach of children. In case of overdose, get medical help or contact a poison control center right away. If pregnant or breastfeeding, ask a healthcare professional before use.

Keep out of the reach of children.

PREGNANCY OR BREAST FEEDING

If pregnant or breastfeeding, ask a healthcare professional before use.

DIRECTIONS

Place drops under tongue 30 minutes before/after meals. Adults and children 12 years and over: Take 10 to 15 drops once weekly or monthly. If mild symptoms are present, take 10 drops up to 3 times per day. Consult a physician for use in children under 12 years of age.

OTHER INFORMATION

Tamper resistant. If seal is broken, do not use. After opening, close container tightly and store at room temperature away from heat.

INACTIVE INGREDIENTS

20% ethanol, purified water.

LABEL

Est 1985

Professional Formulas

Complementary Health

Toxic Fungi-Mold Nosode

Homeopathic Remedy

2 FL. OZ. (59 mL)